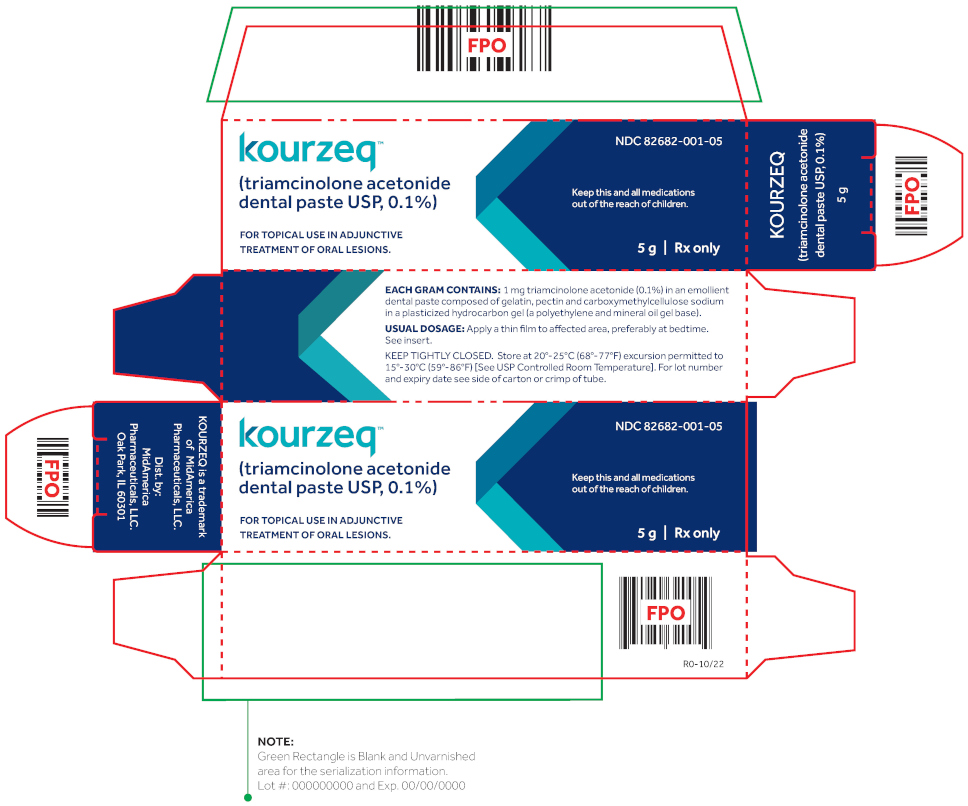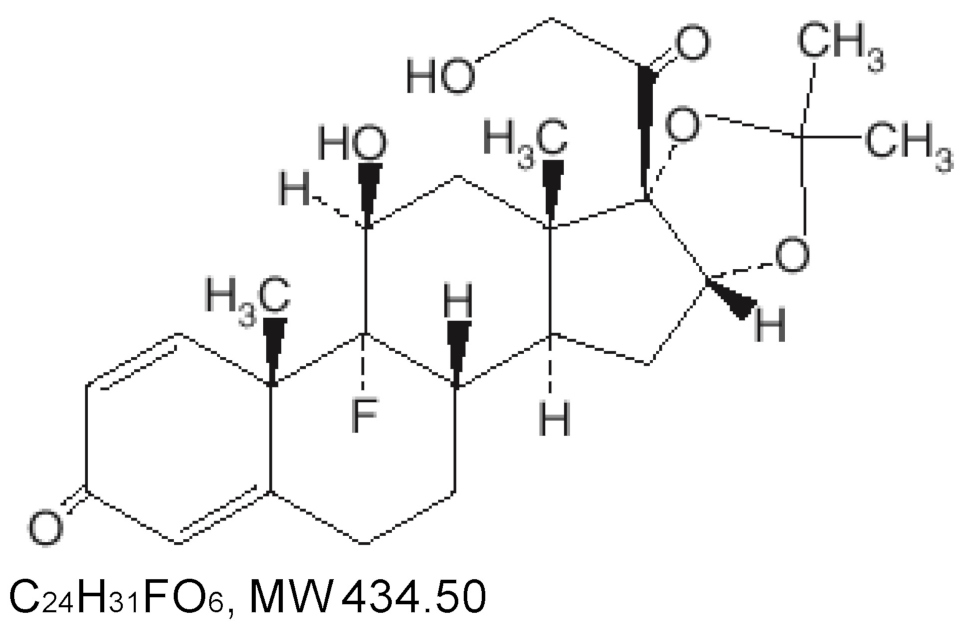 DRUG LABEL: KOURZEQ
NDC: 82682-001 | Form: PASTE
Manufacturer: MidAmerica Pharmaceuticals
Category: prescription | Type: HUMAN PRESCRIPTION DRUG LABEL
Date: 20251118

ACTIVE INGREDIENTS: Triamcinolone Acetonide 1 mg/1 g
INACTIVE INGREDIENTS: gelatin; pectin, citrus; carboxymethylcellulose sodium

KOURZEQ™
(triamcinolone acetonide dental paste USP, 0.1%)

Rx only

DESCRIPTION

KOURZEQ (triamcinolone acetonide dental paste USP, 0.1%) contains the corticosteroid triamcinolone acetonide in an adhesive vehicle suitable for application to oral tissues. Triamcinolone acetonide is designated chemically as 9-fluoro-11β - 16α, 17, 21-tetrahydroxypregna-1, 4-diene-3, 20-dione cyclic 16, 17-acetal with acetone. The structural formula of triamcinolone acetonide is as follows:

Each gram of KOURZEQ contains 1 mg triamcinolone acetonide in a dental paste containing gelatin, pectin, cream flavor, vanilla flavor and carboxymethylcellulose sodium in Plasticized Hydrocarbon Gel, a polyethylene and mineral oil gel base.

CLINICAL PHARMACOLOGY

Like other topical corticosteroids, triamcinolone acetonide has anti-inflammatory, antipruritic, and vasoconstrictive properties. The mechanism of the anti-inflammatory activity of the topical steroids, in general, is unclear. However, corticosteroids are thought to act by the induction of phospholipase A2 inhibitory proteins, collectively called lipocortins. It is postulated that these proteins control the biosynthesis of potent mediators of inflammation such as prostaglandins and leukotrienes by inhibiting the release of their common precursor, arachidonic acid. Arachidonic acid is released from membrane phospholipids by phospholipase A2.

Pharmacokinetics

The extent of absorption through the oral mucosa is determined by multiple factors including the vehicle, the integrity of the mucosal barrier, the duration of therapy, and the presence of inflammation and/or other disease processes. Once absorbed through the mucous membranes, the disposition of corticosteroids is similar to that of systemically administered corticosteroids. Corticosteroids are bound to the plasma proteins in varying degrees. Corticosteroids are metabolized primarily in the liver and are then excreted by the kidneys; some corticosteroids and their metabolites are also excreted into the bile.

INDICATIONS AND USAGE

KOURZEQ is indicated for adjunctive treatment and for the temporary relief of symptoms associated with oral inflammatory lesions and ulcerative lesions resulting from trauma.

CONTRAINDICATIONS

Triamcinolone Acetonide Dental Paste USP, 0.1% is contraindicated in those patients with a history of hypersensitivity to any of the components of the preparations; it is also contraindicated in the presence of fungal, viral, or bacterial infections of the mouth or throat.

PRECAUTIONS

General:
Triamcinolone Acetonide Dental Paste USP, 0.1% may cause local adverse reactions. If irritation develops, Triamcinolone Acetonide Dental Paste USP, 0.1% should be discontinued and appropriate therapy instituted. Allergic contact sensitization with corticosteroids is usually diagnosed by observing failure to heal rather than noting a clinical exacerbation as with most topical products not containing corticosteroids. Such an observation should be corroborated with appropriate diagnostic patch testing.

If concomitant mucosal infections are present or develop, an appropriate antifungal or antibacterial agent should be used. If a favorable response does not occur promptly, use of Triamcinolone Acetonide Dental Paste USP, 0.1% should be discontinued until the infection has been adequately controlled.

If significant regeneration or repair of oral tissues has not occurred in seven days, additional investigation into the etiology of the oral lesion is advised.

Systemic absorption of topical corticosteroids has produced reversible hypothalamic-pituitary-adrenal (HPA) axis suppression, manifestations of Cushing's syn drome, hyperglycemia, glucosuria, and other adverse effects known to occur with parenterally-administered steroid preparations; therefore, it may be advisable to periodically evaluate patients on prolonged therapy with corticosteroidcontaining dental pastes for evidence of HPA axis suppression (see PRECAUTIONS, Laboratory Tests). If HPA axis suppression is noted, an attempt should be made to withdraw the drug or to reduce the frequency of application. Recovery of HPA axis function is generally prompt and complete upon discontinuation of therapy.

PATIENT COUNSELING INFORMATION

Information for the Patient: Patients using topical corticosteroids should receive the following information and instructions:

This medication is to be used as directed by the physician or dentist. It is for oral use only; it is not intended for ophthalmic or dermatological use.

Patients should be advised not to use this medication for any disorder other than for which it was prescribed.

Patients should report any signs of adverse reactions.

As with other corticosteroids, therapy should be discontinued when control is achieved. If no improvement is seen within 2 weeks, contact the physician or dentist.

Laboratory Tests
A urinary free cortisol test and ACTH stimulation test may be helpful in evaluating HPA axis suppression.

Carcinogenesis, Mutagenesis, Impairment of Fertility
Animal studies have not been performed to evaluate triamcinolone acetonide for potential to induce carcinogenesis, mutagenesis, or impairment of fertility.

Teratogenic effects: Triamcinolone acetonide has been shown to induce teratogenic effects in several species. In mice and rabbits, triamcinolone acetonide induced an increased incidence of cleft palate at dosages of approximately 120 mcg/kg/day and 24 mcg/kg/day, respectively (approximately 12 times and 10 times the amount in a typical daily human dose of Triamcinolone Acetonide Dental Paste USP, 0.1 % when compared following normalization of the data on the basis of body surface area estimates, respectively). In monkeys, triamcinolone acetonide induced cranial skeletal malformations at the lowest dosage studied (500 mcg/kg/day), which was approximately 200 times the amount in a typical daily human dose of Triamcinolone Acetonide Dental Paste USP, 0.1 % when compared following normalization of the data on the basis of body surface area estimates. There are no adequate and well-controlled studies in pregnant women. However, a retrospective analysis of birth defects among children born to mothers that used drugs of the same class as Triamcinolone Acetonide Dental Paste USP, 0.1 % (corticosteroids) during pregnancy found an approximately 3 times increased incidence of cleft palate. Triamcinolone Acetonide Dental Paste USP, 0.1 % should be used during pregnancy only if the potential benefit justifies the potential risk to the fetus.

Nursing Mothers
It is not known whether oral application of corticosteroids could result in sufficient systemic absorption to produce detectable quantities in breast milk. Caution should be exercised when corticosteroid-containing dental pastes are prescribed for a nursing woman.

Pediatric Use
The safety and efficacy of Triamcinolone Acetonide Dental Paste USP, 0.1 % in children is unknown. Pediatric patients may demonstrate greater susceptibility to topical corticosteroid induced HPA axis suppression and Cushing's Syndrome than mature patients because of a larger skin surface area to body weight ratio. Administration of corticosteroid containing dental pastes to children should be limited to the least amount compatible with an effective therapeutic regimen. Chronic corticosteroid therapy may interfere with the growth and development of children.

Geriatric Use
Clinical studies of Triamcinolone Acetonide Dental Paste USP, 0.1 % did not include sufficient numbers of subjects age 65 and older to determine whether they respond differently from younger subjects. Other reported clinical experience has not identified differences in responses between the elderly and younger patients.

ADVERSE REACTIONS

The following local adverse reactions may occur with corticosteroid-containing dental pastes: burning, itching, irritation, dryness, blistering or peeling not present prior to therapy, perioral dermatitis, allergic contact dermatitis, maceration of the oral mucosa, secondary infection, and atrophy of the oral mucosa.

Also, see PRECAUTIONS for potential effects of systemic absorption.

DOSAGE AND ADMINISTRATION

Press a small dab (about ¼ inch) to the lesion until a thin film develops. A larger quantity may be required for coverage of some lesions. For optimal results use only enough to coat the lesion with a thin film. Do not rub in. Attempting to spread this preparation may result in granular, gritty sensation and cause it to crumble. After application, however, a smooth, slippery film develops.

The preparation should be applied at bedtime to permit steroid contact with the lesion throughout the night. Depending on the severity of symptoms, it may be necessary to apply the preparation two or three times a day, preferably after meals. If significant repair or regeneration has not occurred in seven days, further investigation is advisable.

HOW SUPPLIED

KOURZEQ (triamcinolone acetonide dental paste USP, 0.1%) is supplied in tubes containing 5 g of dental paste
NDC 82682-001-05

Storage
Keep tightly closed. Store at 20° – 25° C (68° – 77° F) excursion permitted to 15° – 30° C (59° – 86° F) [See USP Controlled Room Temperature].

Distributed by:
MidAmerica Pharmaceuticals, LLC
Oak Park, IL 60301

Manufactured by:
Lyne Laboratories, Inc.
Brockton, MA 02301

R0-10/22

KOURZEQTM is a trademark of MidAmerica Pharmaceuticals, LLC.

Principal Display Panel – Carton Label

kourzeq TM NDC 82682-001-05

(triamcinolone acetonide
dental paste USP, 0.1%)

FOR TOPICAL USE IN ADJUNTIVE
TREATMENT OF ORAL LESIONS.

Keep this and all medications
out of the reach of children.

5 g | Rx only